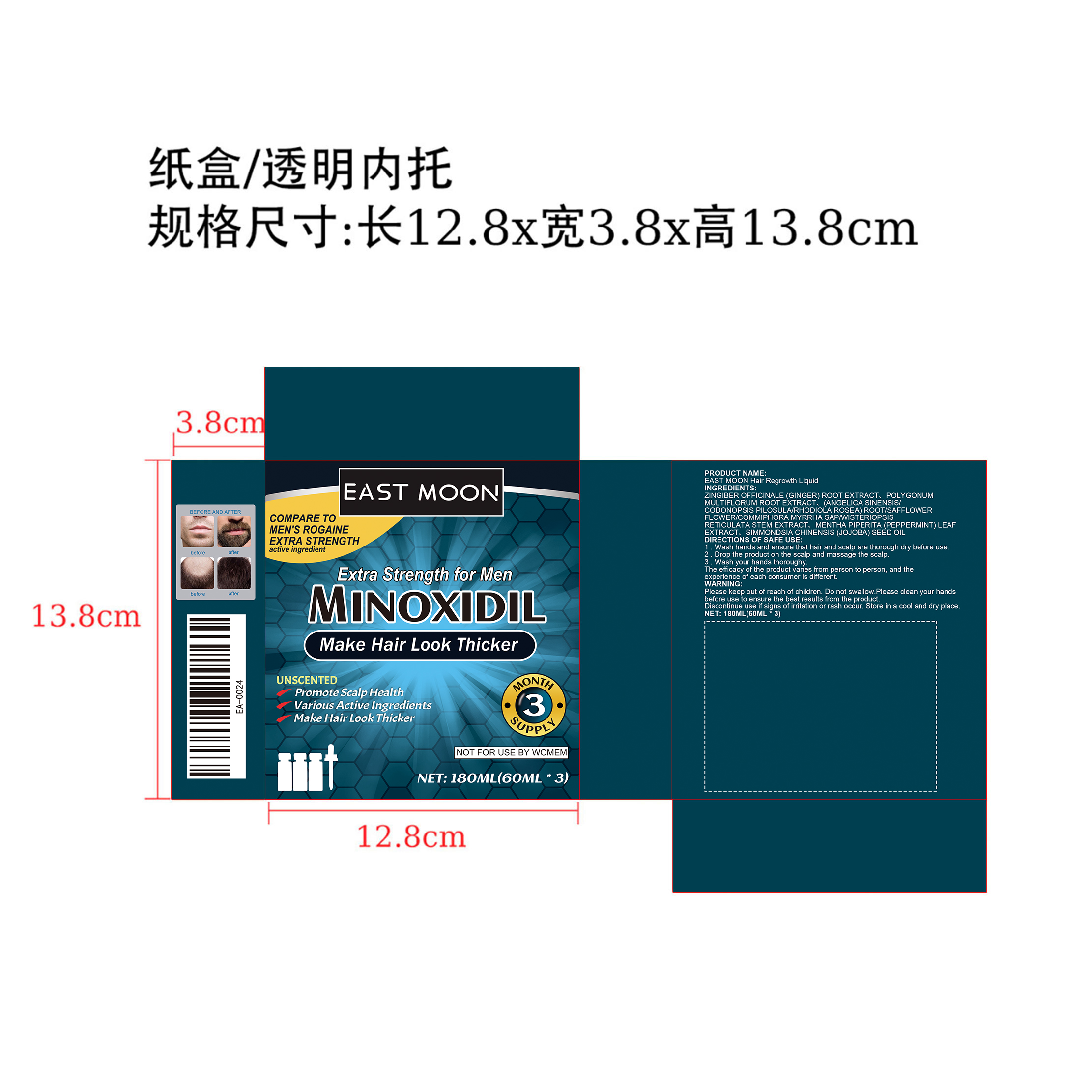 DRUG LABEL: east moon hair regrowth liquid
NDC: 84372-050 | Form: LOTION
Manufacturer: Shenzhen Zhumeng Times Technology Co., Ltd.
Category: otc | Type: HUMAN OTC DRUG LABEL
Date: 20240909

ACTIVE INGREDIENTS: FALLOPIA MULTIFLORA ROOT 5 g/60 mL
INACTIVE INGREDIENTS: ANGELICA DAHURICA VAR. FORMOSANA ROOT; GINGER; JOJOBA OIL

Active ingredients

POLYGONUMMULTIFLORUM ROOT EXTRACT 5%

Purpose

Halr regrowth treatment for men

Uses

Wash hands and ensure that hair and scalp are thorough dry before use.2.

Drop the product on the scalp and massage the scalp.3.

Wash your hands thoroughy.

The efficacy of the product varies from person to person, and the experience of each consumer is different.

Warnings

Please keep out of reach of children.

Do not swallow.

Please clean your handsbefore use to ensure the best results from the product.

Discontinue use if signs of irritation or rash occur.

Store in a cool and dry place.

Dosage and administration

For external use only.

Do not use

Stop use and ask a doctor if

chest pain, rapid heartbeat, faintness, or dizziness occurs

sudden, unexplained weight gain occurs

your hands or feet swell

scalp irritation or redness occurs

unwanted facial hair growth occurs

you do not see hair regrowth in 4 months

May be harmful if used when pregnant or breast-feeding.

Keep out of reach of children, lf swallowed, get medical help or contact a Poison Control Center right away.

When using section

do not apply on other parts of the body

avoid contact with the eyes. in case of accidental contact, rinse eyes with large amounts of cool tap water

some people have experienced changes in hair color and/or texture

it takes time to regrow hair. Results may occur at 2 months with twice a day usage. For some people, you may need to use this product for at least 4 months before you see results.the amount of hair regrowth is different for each person. This product will notwork for all men.

stop use

Broken or inflamed body

Keep out of reach of children.

If sxralowed, get medical help or contact a Poison Conirol Cenler ngiht away

Inactive ingredients

ZINGIBER OFFICINALE (GINGER) ROOT EXTRACT、POLYGONUMMULTIFLORUM ROOT EXTRACT、 (ANGELICA SINENSIS/ CODONOPSIS PILOSULA/RHODIOLA ROSEA) ROOT/SAFFLOWER FLOWER/COMMIPHORA MYRRHA SAPWISTERIOPSIS RETICULATA STEM EXTRACT,MENTHA PIPERITA (PEPPERMINT) LEAF EXTRACT、 SIMMONDSIA CHINENSIS (JOJOBA) SEED OIL